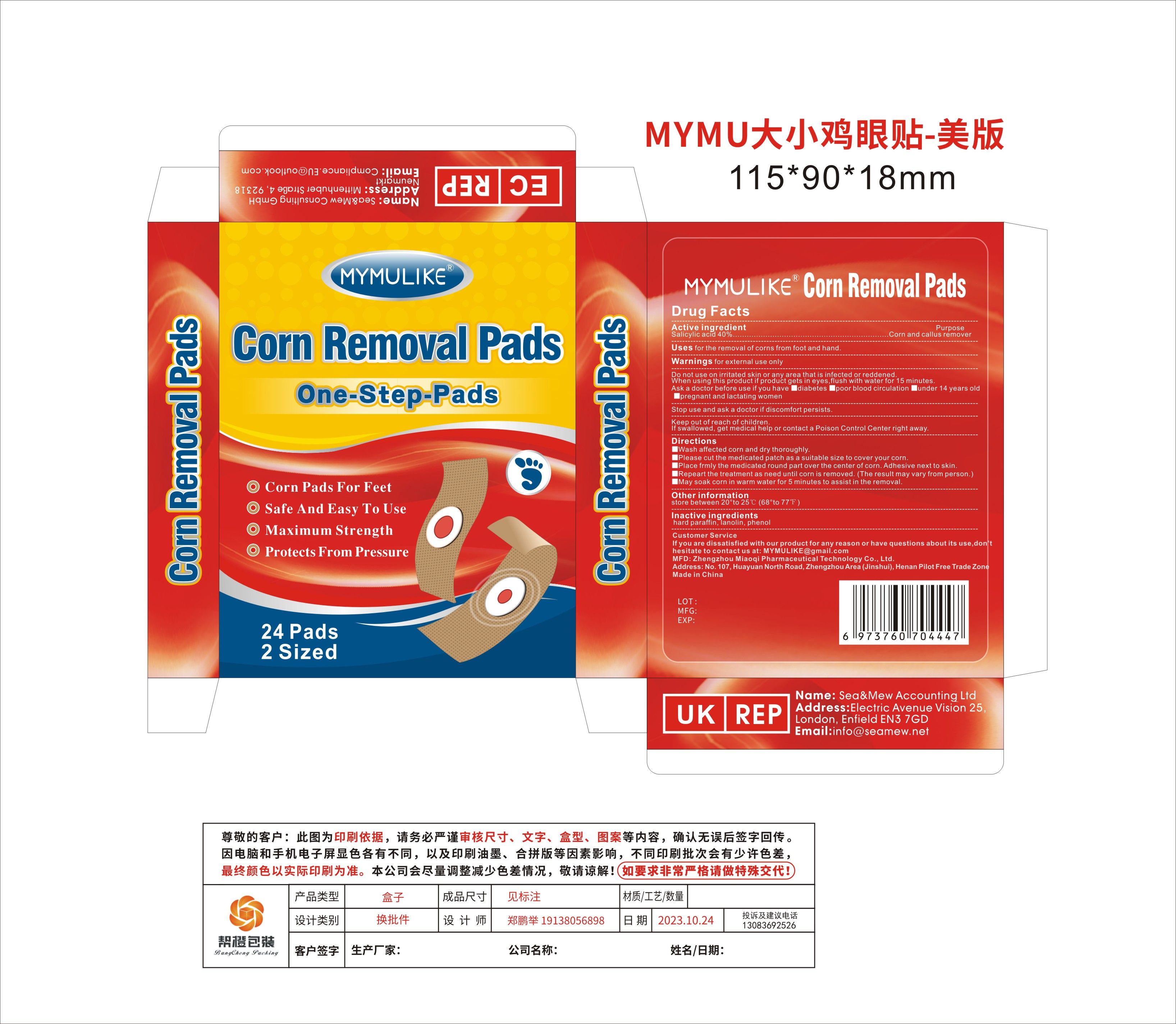 DRUG LABEL: MYMULIKE Corn Removal Pads
NDC: 83781-003 | Form: PATCH
Manufacturer: Zhengzhou Miaoqi Pharmaceutical Technology Co., Ltd
Category: otc | Type: HUMAN OTC DRUG LABEL
Date: 20250324

ACTIVE INGREDIENTS: SALICYLIC ACID 40 g/100 1
INACTIVE INGREDIENTS: PARAFFIN; PHENOL; LANOLIN

83781-003 Updete V2

Active Ingredient

Salicylic acid 40%

Purpose

Corn and callus remover

Use

for the removal of corns from foot and hand.

Warnings

for external use only

Do not use

on irritated skin or any area that is infected or reddened.

When Using

if product gets in eyes,flush with water for 15 minutes.
Ask a doctor before use if you have

■diabetes

■poor blood circulation

■under 14 years old

■pregnant and lactating women

Stop Use

discomfort persists.

Ask Doctor

discomfort persists.

Keep Out Of Reach Of Children

If swallowed, get medical help or contact a Poison Control Center right away.

Directions

■Wash affected corn and dry thoroughly.

■Please cut the medicated patch as a suitable size to cover your corn.

■Place frmly the medicated round part over the center of corn. Adhesive next to skin.

■Repeart the treatment as need until corn is removed. (The result may vary from person.)

■May soak corn in warm water for 5 minutes to assist in the removal.

Other information

store between 20°to 25℃ (68°to 77℉)

Inactive ingredients

hard paraffin, lanolin, phenol

Questions

MYMULIKE@gmail.com